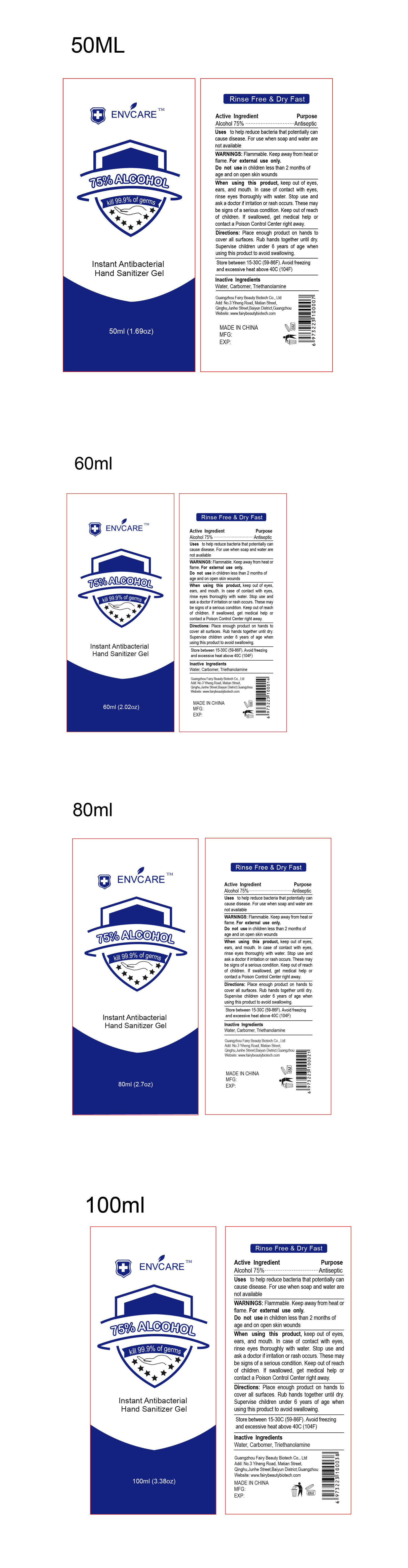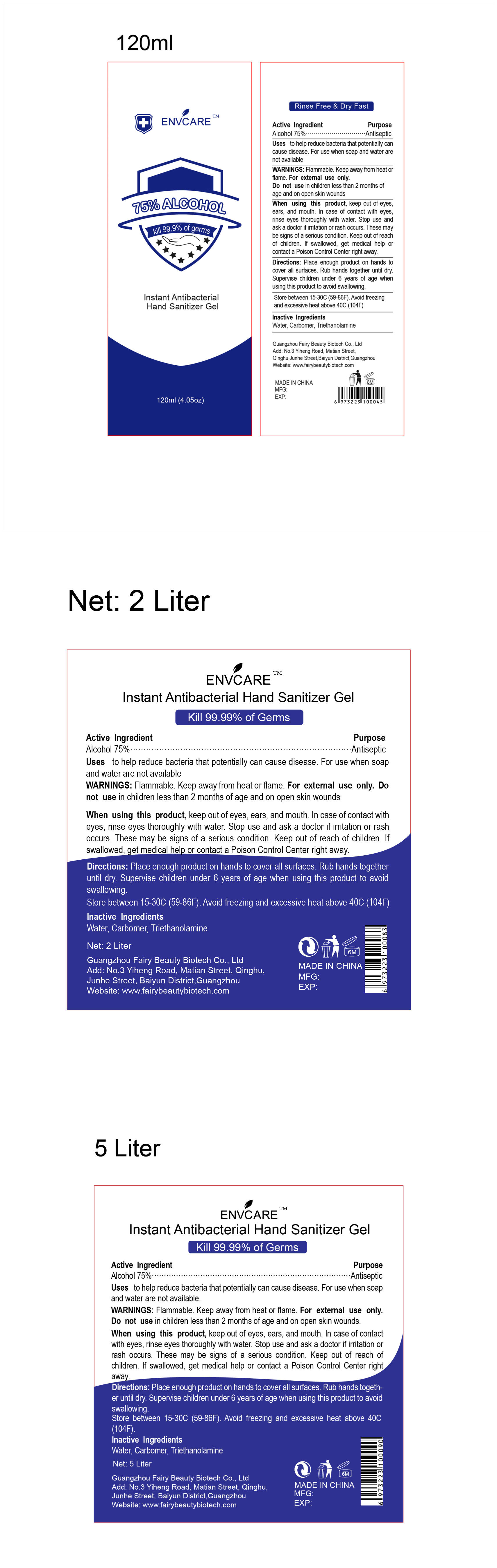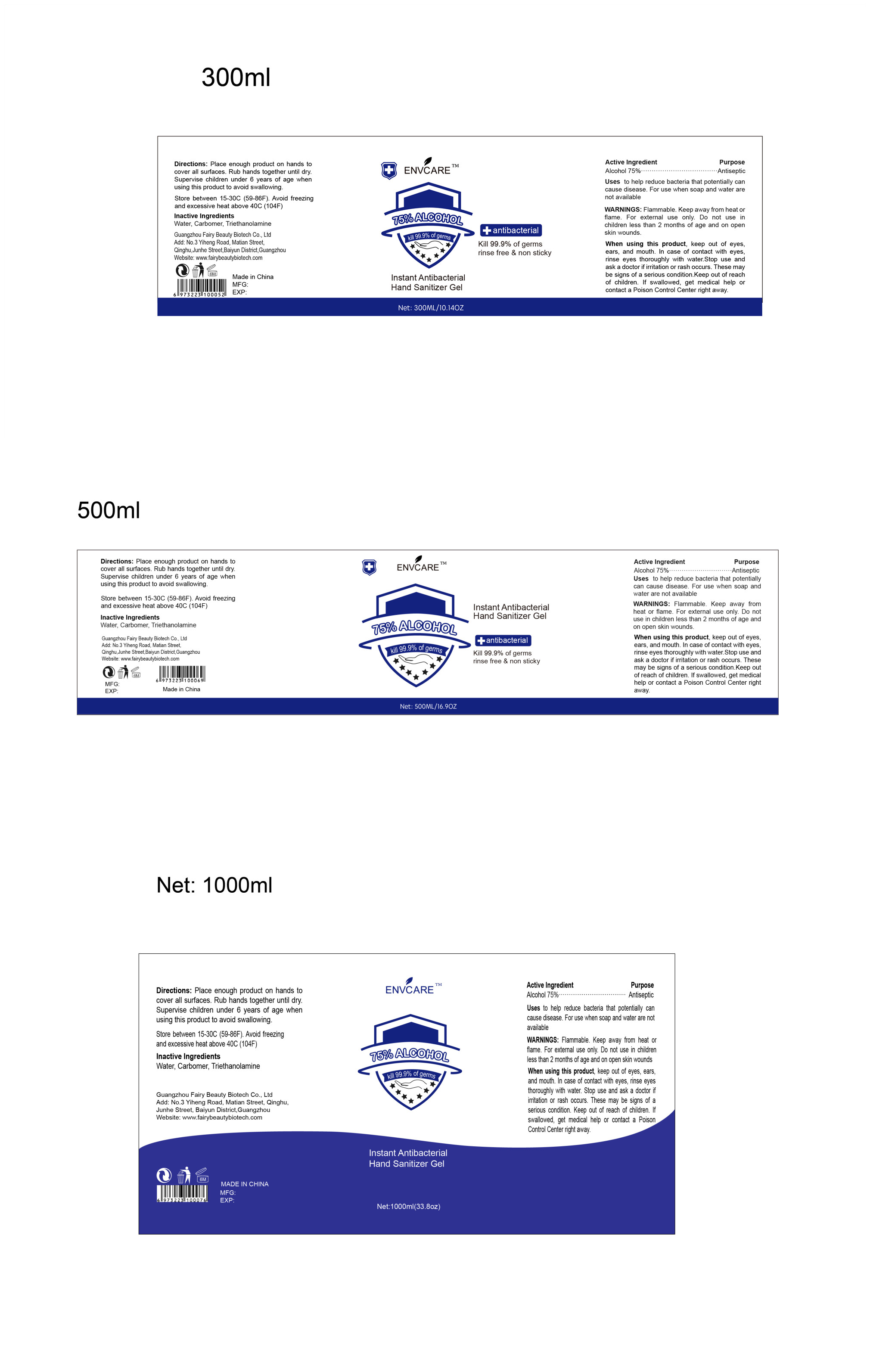 DRUG LABEL: Instant Antibacterial Hand Sanitizer Gel
NDC: 75703-005 | Form: GEL
Manufacturer: Guangzhou Fairy Beauty Biotech Co., Ltd
Category: otc | Type: HUMAN OTC DRUG LABEL
Date: 20200510

ACTIVE INGREDIENTS: ALCOHOL 80 mL/100 mL
INACTIVE INGREDIENTS: TROLAMINE; CARBOMER HOMOPOLYMER TYPE C (ALLYL PENTAERYTHRITOL CROSSLINKED); WATER

Instant Antibacterial Hand Sanititizer Gel

Active Ingredient(s)

Alcohol 75% v/v. Purpose: Antiseptic

Purpose

Antiseptic, Hand Sanitizer

Use

Uses to help reduce bacteria that potentially cancause disease. For use when soap and water arenot available

Warnings

Flammable. Keep away from heat or flame。 For externail use only

- Do not use in children less than 2 months of age and on open skin wounds

When using this product, keep out of eyes,ears, and mouth. In case of contact with eye srinse eyes thoroughly with water.

Stop use

Stop use and ask a doctor if irritation or rash occurs. These may be signs of a serious condition

KEEP OUT OF REACH OF CHILDREN

. Keep out of reachof children. If swallowed, get medical help or contact a Poison Control Center right away

Directions

- Directions: Place enough product on hands tocover all surfaces. Rub hands together until dry Supervise children under 6 years of age when using this product to avoid swallow

Other information

- Store between 15-30C(59-86F)
- Avoid freezingand excessive heat above 40C(104F)

Inactive ingredients

Water Carbomer. Triethanolamine